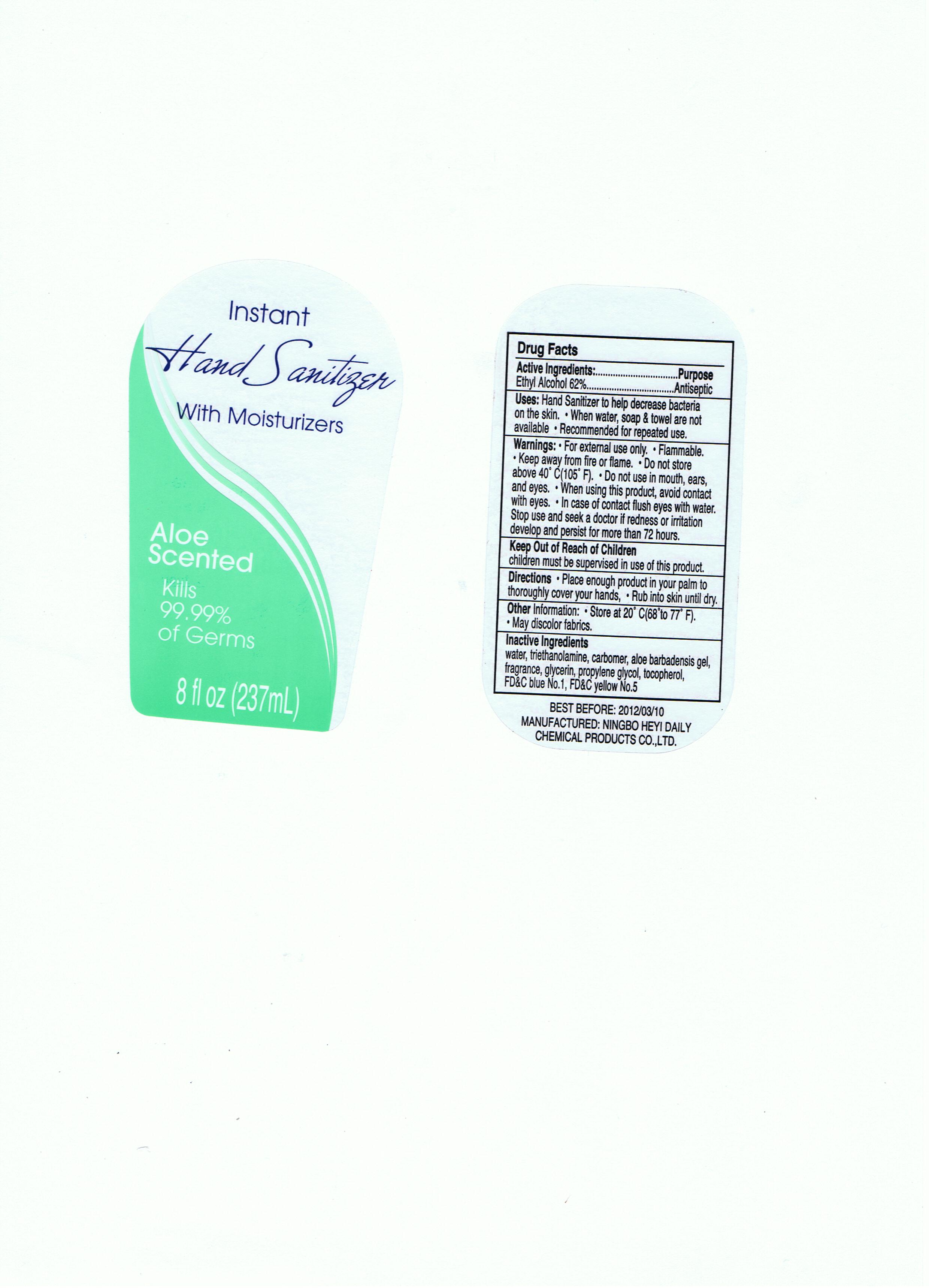 DRUG LABEL: Instant Hand Sanitizer with Moisturizers Aloe Scented
NDC: 51335-002 | Form: LIQUID
Manufacturer: Ningbo Heyi Daily Chemical Products Co., Ltd.
Category: otc | Type: HUMAN OTC DRUG LABEL
Date: 20100809

ACTIVE INGREDIENTS: ALCOHOL 62 g/100 g
INACTIVE INGREDIENTS: WATER 34.29 g/100 g; PROPYLENE GLYCOL 2.257 g/100 g; TROLAMINE 0.375 g/100 g; CARBOMER HOMOPOLYMER TYPE A 0.3 g/100 g; ALOE VERA LEAF 0.007 g/100 g; GLYCERIN 0.315 g/100 g; ALPHA-TOCOPHEROL 0.006 g/100 g; FD&C BLUE NO. 1 0.02 g/100 g; FD&C YELLOW NO. 5 0.02 g/100 g

Drug Fact

Active Ingredient

Ethyl Alcohol 62%

Purpose:

Antiseptic

Uses:
* Hand Sanitizer to help decrease bacteria on the skin.
* When water, soap and towel are not available
* Recommended for repeated use.

Warnings:
For external use only
Flammable
Keep away from fire or flame
Do not store above 40 C (105F)
Do not use in mouth, ears, and eyes
When using this product, avoid contact with eyes
In case of contact, flush eyes with water
Stop use and seek a doctor if redness or irritation develop and persist for more than 72 hours.

Keep out of Reach of Children
Children must be supervised in use of this product

Directions:
Place enough product in your palm to thoroughly cover your hands
Rub into skin until dry

Other Information
Store at 20C (68-77F)
May discolor fabrics

Inactive Ingredients:
Water, Triethanolamine, Carbomer, Aloe Barbadensis Gel, Glycerin, Propylene Glycol, Tocopherol, FD and C Blue No. 1, FD and C Yellow No. 5

PACKAGE LABEL

labe